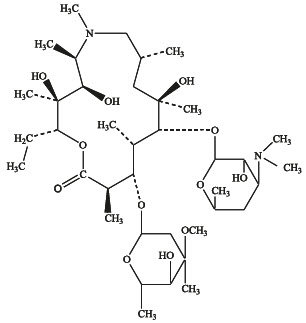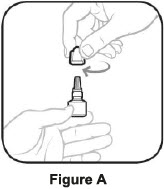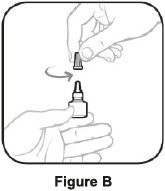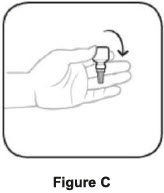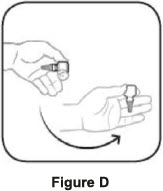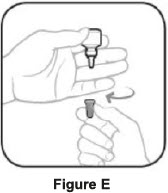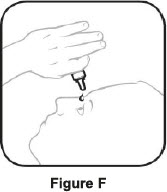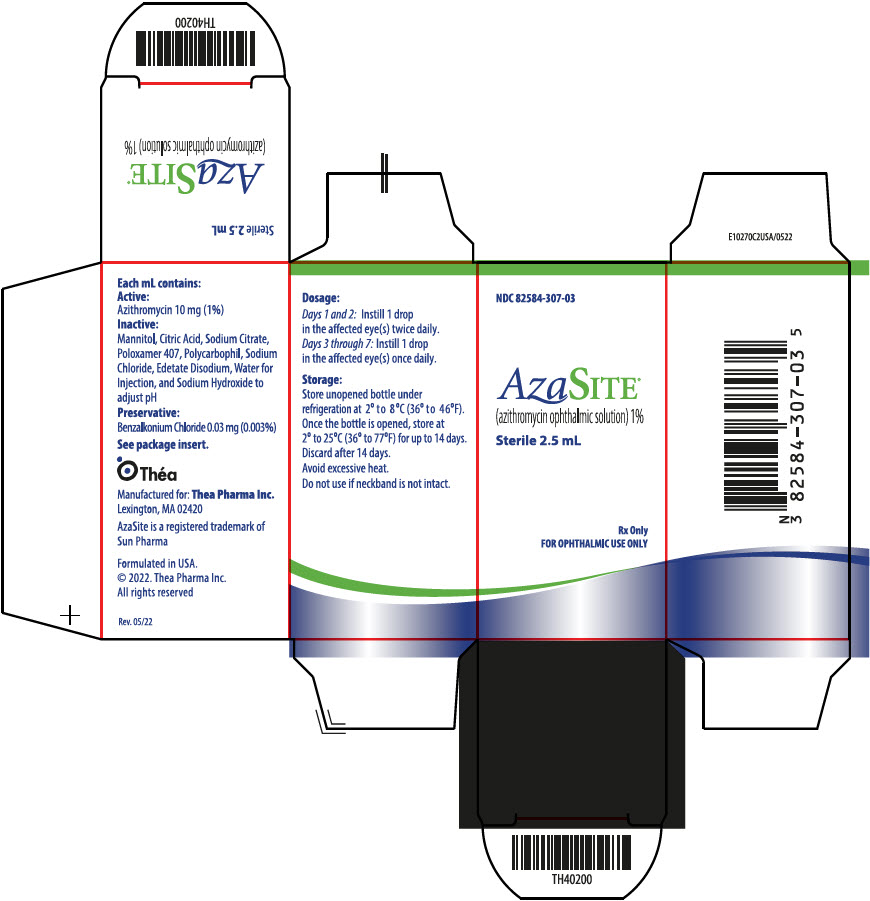 DRUG LABEL: AZASITE
NDC: 82584-307 | Form: SOLUTION/ DROPS
Manufacturer: Thea Pharma Inc.
Category: prescription | Type: HUMAN PRESCRIPTION DRUG LABEL
Date: 20240725

ACTIVE INGREDIENTS: AZITHROMYCIN MONOHYDRATE 10 mg/1 mL
INACTIVE INGREDIENTS: BENZALKONIUM CHLORIDE 0.03 mg/1 mL; MANNITOL; CITRIC ACID MONOHYDRATE; SODIUM CITRATE, UNSPECIFIED FORM; POLOXAMER 407; POLYCARBOPHIL; SODIUM CHLORIDE; EDETATE DISODIUM; WATER; SODIUM HYDROXIDE

HIGHLIGHTS OF PRESCRIBING INFORMATION

These highlights do not include all the information needed to use AzaSite safely and effectively. See full prescribing information for AzaSite.
AzaSite® (azithromycin ophthalmic solution) 1%
Sterile topical ophthalmic drops
Initial U.S. Approval: 2007

1 INDICATIONS AND USAGE

AzaSite is a macrolide antimicrobial indicated for the treatment of bacterial conjunctivitis caused by susceptible isolates of the following microorganisms: CDC coryneform group G, Haemophilus influenzae, Staphylococcus aureus, Streptococcus mitis group, and Streptococcus pneumoniae. (1)

2 DOSAGE AND ADMINISTRATION

Instill 1 drop in the affected eye(s) twice daily, eight to twelve hours apart for the first two days and then instill 1 drop in the affected eye(s) once daily for the next five days. (2)

3 DOSAGE FORMS AND STRENGTHS

2.5 mL of 1% sterile topical ophthalmic solution. (3)

4 CONTRAINDICATIONS

Hypersensitivity (4)

5 WARNINGS AND PRECAUTIONS

- For topical ophthalmic use only. (5.1)
- Anaphylaxis and hypersensitivity have been reported with systemic use of azithromycin. (5.2)
- Growth of resistant organisms may occur with prolonged use. (5.3)
- Patients should not wear contact lenses if they have signs or symptoms of bacterial conjunctivitis. (5.4)

6 ADVERSE REACTIONS

Most common adverse reaction reported in patients was eye irritation (1 to 2% of patients). (6)

To report SUSPECTED ADVERSE REACTIONS, contact Thea Pharma Inc. at 1-833-838-4028 or FDA at 1-800-FDA-1088 or www.fda.gov/medwatch.

See 17 for PATIENT COUNSELING INFORMATION and FDA-approved patient labeling.

FULL PRESCRIBING INFORMATION

1 INDICATIONS AND USAGE

AzaSite® is indicated for the treatment of bacterial conjunctivitis caused by susceptible isolates of the following microorganisms:

CDC coryneform group G [Efficacy for this organism was studied in fewer than 10 infections.]
Haemophilus influenzae
Staphylococcus aureus
Streptococcus mitis group
Streptococcus pneumoniae

2 DOSAGE AND ADMINISTRATION

The recommended dosage regimen for the treatment of bacterial conjunctivitis is:

Instill 1 drop in the affected eye(s) twice daily, eight to twelve hours apart for the first two days and then instill 1 drop in the affected eye(s) once daily for the next five days.

2.1 Recommended Dosage

The recommended dosage for the treatment of bacterial conjunctivitis is:

Instill 1 drop in the affected eye(s) twice daily, eight to twelve hours apart for the first two days and then instill 1 drop in the affected eye(s) once daily for the next five days.

2.2 Administration Instructions

Wash hands prior to using AzaSite.

Invert the closed bottle (upside down) and shake once before each use. Remove the tan cap with the bottle still in the inverted position. Tilt head back, and with bottle inverted, gently squeeze bottle to instill one drop into the affected eye(s).

Skipping doses or not completing the full course of therapy may (1) decrease the effectiveness of the immediate treatment and (2) increase the likelihood that bacteria will develop resistance and will not be treatable by AzaSite (azithromycin ophthalmic solution) or other antibacterial drugs in the future.

3 DOSAGE FORMS AND STRENGTHS

2.5 mL of a 1% sterile topical ophthalmic solution.

4 CONTRAINDICATIONS

Azasite is contraindicated in patients with hypersensitivity to any component of this product.

5 WARNINGS AND PRECAUTIONS

5.1 Topical Ophthalmic Use Only

NOT FOR INJECTION. AzaSite is indicated for topical ophthalmic use only, and should not be administered systemically, injected subconjunctivally, or introduced directly into the anterior chamber of the eye.

5.2 Anaphylaxis and Hypersensitivity with Systemic Use of Azithromycin

In patients receiving systemically administered azithromycin, serious allergic reactions, including angioedema, anaphylaxis, and dermatologic reactions including Stevens-Johnson syndrome and toxic epidermal necrolysis have been reported rarely in patients on azithromycin therapy. Although rare, fatalities have been reported. The potential for anaphylaxis or other hypersensitivity reactions should be considered based on known hypersensitivity to azithromycin when administered systemically.

5.3 Growth of Resistant Organisms with Prolonged Use

As with other anti-infectives, prolonged use may result in overgrowth of non-susceptible organisms, including fungi. If super-infection occurs, discontinue use and institute alternative therapy. Whenever clinical judgment dictates, the patient should be examined with the aid of magnification, such as slit-lamp biomicroscopy, and where appropriate, fluorescein staining.

5.4 Contamination of the Applicator Tip

Avoid contaminating the applicator tip by not allowing it to touch the eye, fingers or other sources.

5.5 Avoidance of Contact Lenses

Patients should be advised not to wear contact lenses if they have signs or symptoms of bacterial conjunctivitis.

6 ADVERSE REACTIONS

Because clinical trials are conducted under widely varying conditions, adverse reaction rates observed in one clinical trial of a drug cannot be directly compared with the rates in the clinical trials of the same or another drug and may not reflect the rates observed in practice.

The data described below reflect exposure to AzaSite in 698 patients. The population was between 1 and 87 years old with clinical signs and symptoms of bacterial conjunctivitis. The most frequently reported ocular adverse reaction reported in patients receiving AzaSite was eye irritation. This reaction occurred in approximately 1 to 2% of patients. Other adverse reactions associated with the use of AzaSite were reported in less than 1% of patients and included ocular reactions (blurred vision, burning, stinging and irritation upon instillation, contact dermatitis, corneal erosion, dry eye, eye pain, itching, ocular discharge, punctate keratitis, visual acuity reduction) and non-ocular reactions (dysgeusia, facial swelling, hives, nasal congestion, periocular swelling, rash, sinusitis, urticaria).

8 USE IN SPECIFIC POPULATIONS

8.1 Pregnancy

TERATOGENIC EFFECTS

Risk Summary

Available data from published literature and postmarketing experience over several decades with azithromycin use in pregnant women have not identified any drug-associated risks for major birth defects, miscarriage, or adverse maternal or fetal outcomes (see Data). Developmental toxicity studies with azithromycin in rats, mice, and rabbits showed no drug-induced fetal malformations at doses up to 200 mg/kg/day. The doses used in these studies were orders of magnitude in excess of the clinical exposure that would be possible following topical ocular administration of azithromycin. (see Data).

The estimated background risk of major birth defects and miscarriage for the indicated populations is unknown. All pregnancies have a background risk of birth defect, loss, or other adverse outcomes. In the U.S. general population, the estimated background risk of major birth defects and miscarriage in clinically recognized pregnancies is 2 to 4% and 15 to 20%, respectively.

Data

Human Data

Available data from published observational studies, case series, and case reports over several decades do not suggest an increased risk for major birth defects, miscarriage, or adverse maternal or fetal outcomes with oral or topical ophthalmic azithromycin use in pregnant women. Limitations of these data include the lack of randomization and inability to control for confounders such as underlying maternal disease and maternal use of concomitant medications.

Animal Data

Azithromycin administered during the period of organogenesis did not cause fetal malformations in rats and mice at oral doses up to 200 mg/kg/day (moderately maternally toxic). Assuming 100% absorption from topical ocular exposure, this dose is hundreds of times daily dose that can be achieved with topical ophthalmic administration. In rabbits administered azithromycin at oral doses of 10, 20, and 40 mg/kg/day during organogenesis, reduced maternal body weight and food consumption were observed in all groups; no evidence of fetotoxicity or teratogenicity was observed at these doses, the highest of which is estimated to be at least 100 times topical ophthalmic dose assuming 100% absorption from ocular exposure.

In a pre- and postnatal development study, azithromycin was administered orally to pregnant rats from day 6 of pregnancy until weaning at doses of 50 or 200 mg/kg/day. Maternal toxicity (reduced food consumption and body weight gain; increased stress at parturition) was observed at the higher dose. Effects in the offspring were noted at 200 mg/kg/day during the postnatal development period (decreased viability, delayed developmental landmarks). These effects were not observed in a pre- and postnatal rat study when up to 200 mg/kg/day of azithromycin was given orally beginning on day 15 of pregnancy until weaning. Assuming 100% absorption from topical ocular exposure, this dose is hundreds of times daily dose that can be achieved with topical ophthalmic administration.

8.2 Lactation

Risk Summary

Azithromycin is present in human milk (see Data). Non-serious adverse reactions have been reported in breastfed infants after maternal administration of oral azithromycin. There are no available data on the effects of azithromycin on milk production. The developmental and health benefits of breastfeeding should be considered along with the mother’s clinical need for AzaSite and any potential adverse effects on the breastfed infant from AzaSite.

Data

Azithromycin breastmilk concentrations were measured in 20 women after receiving a single 2 g oral dose of azithromycin during labor. Breastmilk samples collected on days 3 and 6 postpartum as well as 2 and 4 weeks postpartum revealed the presence of azithromycin in breastmilk up to 4 weeks after dosing. In another study, a single dose of azithromycin 500 mg was administered intravenously to 8 women prior to incision for cesarean section. Breastmilk (colostrum) samples obtained between 12 and 48 hours after dosing revealed that azithromycin persisted in breastmilk up to 48 hours.

8.4 Pediatric Use

The safety and effectiveness of AzaSite solution in pediatric patients have been established. The efficacy of AzaSite in treating bacterial conjunctivitis in pediatric patients has been demonstrated in controlled clinical trials [see Clinical Studies (14)] .

8.5 Geriatric Use

No overall differences in safety or effectiveness have been observed between elderly and younger patients.

11 DESCRIPTION

AzaSite® (azithromycin ophthalmic solution) is a 1% sterile aqueous topical ophthalmic solution of azithromycin formulated in DuraSite® (polycarbophil, edetate disodium, sodium chloride). AzaSite is an off-white, viscous liquid with an osmolality of approximately 290 mOsm/kg.

Preservative: 0.003% benzalkonium chloride. Inactives: mannitol, citric acid, sodium citrate, poloxamer 407, polycarbophil, edetate disodium (EDTA), sodium chloride, water for injection, and sodium hydroxide to adjust pH to 6.3.

Azithromycin is a macrolide antibiotic with a 15-membered ring. Its chemical name is (2R,3S,4R,5R,8R,10R,11R,12S,13S,14R)-13-[(2,6-dideoxy-3-C-methyl-3-O-methyl-α-L-ribohexopyranosyl)oxy]-2-ethyl-3,4,10-trihydroxy-3,5,6,8,10,12,14-heptamethyl-11-[[3,4,6-trideoxy-3-(dimethylamino)-β-D-xylo-hexopyranosyl]oxy]-1-oxa-6-aza-cyclopentadecan-15-one, and the structural formula is:

Azithromycin has a molecular weight of 749, and its empirical formula is C38H72N2O12.

12 CLINICAL PHARMACOLOGY

12.1 Mechanism of Action

Azithromycin is a macrolide antibiotic [see Clinical Pharmacology (12.4)] .

12.3 Pharmacokinetics

The plasma concentration of azithromycin following ocular administration of AzaSite (azithromycin ophthalmic solution) in humans is unknown. Based on the proposed dose of one drop to each eye (total dose of 100 mcL or 1 mg) and exposure information from systemic administration, the systemic concentration of azithromycin following ocular administration is estimated to be below quantifiable limits (≤10 ng/mL) at steady-state in humans, assuming 100% systemic availability.

12.4 Microbiology

Azithromycin acts by binding to the 50S ribosomal subunit of susceptible microorganisms and interfering with microbial protein synthesis.

Azithromycin has been shown to be active against most isolates of the following microorganisms, both in vitro and clinically in conjunctival infections [see Indications and Usage (1)] .

CDC coryneform group G [Efficacy for this organism was studied in fewer than 10 infections.]
Haemophilus influenzae
Staphylococcus aureus
Streptococcus mitis group
Streptococcus pneumoniae

The following in vitro data are also available, but their clinical significance in ophthalmic infections is unknown. The safety and effectiveness of AzaSite in treating ophthalmological infections due to these microorganisms have not been established.

The following microorganisms are considered susceptible when evaluated using systemic breakpoints. However, a correlation between the in vitro systemic breakpoint and ophthalmological efficacy has not been established. This list of microorganisms is provided as an aid only in assessing the potential treatment of conjunctival infections. Azithromycin exhibits in vitro minimal inhibitory concentrations (MICs) of equal or less (systemic susceptible breakpoint) against most (≥90%) of isolates of the following ocular pathogens:

Chlamydia pneumoniae
Chlamydia trachomatis
Legionella pneumophila
Moraxella catarrhalis
Mycoplasma hominis
Mycoplasma pneumoniae
Neisseria gonorrhoeae
Peptostreptococcus species
Streptococci (Groups C, F, G)
Streptococcus pyogenes
Streptococcus agalactiae
Ureaplasma urealyticum
Viridans group streptococci

13 NONCLINICAL TOXICOLOGY

13.1 Carcinogenesis, Mutagenesis, Impairment of Fertility

Long-term studies in animals have not been performed to evaluate carcinogenic potential. Azithromycin has shown no mutagenic potential in standard laboratory tests: mouse lymphoma assay, human lymphocyte clastogenic assay, and mouse bone marrow clastogenic assay. No evidence of impaired fertility due to azithromycin was found in mice or rats that received oral doses of up to 200 mg/kg/day.

13.2 Animal Toxicology and/or Pharmacology

Phospholipidosis (intracellular phospholipid accumulation) has been observed in some tissues of mice, rats, and dogs given multiple systemic doses of azithromycin. Cytoplasmic microvacuolation, which is likely a manifestation of phospholipidosis, has been observed in the corneas of rabbits given multiple ocular doses of AzaSite. This effect was reversible upon cessation of AzaSite treatment. The significance of this toxicological finding for animals and for humans is unknown.

14 CLINICAL STUDIES

In a randomized, vehicle-controlled, double-blind, multicenter clinical study in which patients were dosed twice daily for the first two days, then once daily on days 3, 4, and 5, AzaSite solution was superior to vehicle on days 6 to 7 in patients who had a confirmed clinical diagnosis of bacterial conjunctivitis. Clinical resolution was achieved in 63% (82/130) of patients treated with AzaSite versus 50% (74/149) of patients treated with vehicle. The p-value for the comparison was 0.03 and the 95% confidence interval around the 13% (63% to 50%) difference was 2% to 25%. The microbiological success rate for the eradication of the baseline pathogens was approximately 88% compared to 66% of patients treated with vehicle (p<0.001, confidence interval around the 22% difference was 13% to 31%). Microbiologic eradication does not always correlate with clinical outcome in anti-infective trials.

16 HOW SUPPLIED/STORAGE AND HANDLING

AzaSite® is a sterile aqueous topical ophthalmic formulation of 1% azithromycin.

NDC 82584-307-03: 2.5 mL in 5 mL bottle containing a total of 25 mg of azithromycin in a white, oblong, low-density polyethylene (LDPE) bottle, with a clear LDPE dropper tip, and a tan colored high density polyethylene (HDPE) eyedropper cap. A white tamper evident over-cap is provided.

Storage and Handling

Store unopened bottle under refrigeration at 2° to 8°C (36° to 46°F). Once the bottle is opened, store at 2° to 25°C (36° to 77°F) for up to 14 days. Discard after the 14 days.

The white tamper evident over-cap can be thrown away. Retain the tan cap and keep the bottle tightly closed when not in use.

17 PATIENT COUNSELING INFORMATION

See FDA-Approved Patient Labeling (Patient Information and Instructions for Use).

Avoiding Contamination of the Applicator Tip

Advise patients to avoid contaminating the applicator tip by not allowing it to touch the eye, fingers or other sources.

When to Seek Physician Advice

Direct patients to discontinue use and contact a physician if any signs of an allergic reaction occur.

Tell patients that although it is common to feel better early in the course of the therapy, the medication should be taken exactly as directed. Skipping doses or not completing the full course of therapy may (1) decrease the effectiveness of the immediate treatment and (2) increase the likelihood that bacteria will develop resistance and will not be treatable by AzaSite (azithromycin ophthalmic solution) or other antibacterial drugs in the future.

Contact Lens Use

Advise patients not to wear contact lenses if they have signs or symptoms of bacterial conjunctivitis.

Administration Instructions

Advise patients to thoroughly wash hands prior to using AzaSite.

Advise patients to invert the closed bottle (upside down) and shake once before each use. Remove cap with bottle still in the inverted position. Tilt head back, and with bottle inverted, gently squeeze bottle to instill one drop into the affected eye(s).

Manufactured for: Thea Pharma Inc.
Waltham, MA 02451

U.S. Patent No.: 7,758,553

AzaSite is a registered trademark of Thea Pharma Inc.

DuraSite is a registered trademark of Sun Pharma.
© 2024. Thea Pharma Inc.
All rights reserved

Revised: 07/2024

PATIENT INFORMATION

AzaSite® (A-zuh-site)
(azithromycin ophthalmic solution) 1%

Read this Patient Information before you start using AzaSite® and each time you get a refill. There may be new information. This information does not take the place of talking to your doctor about your medical condition or treatment.

What is AzaSite?

AzaSite is a prescription sterile eye drop solution. AzaSite is used to treat bacterial conjunctivitis which is an infection of the eye caused by certain bacteria.

Information about bacterial conjunctivitis.

Bacterial conjunctivitis is a bacterial infection of the mucous membranes which line the inside of the eyelids. Symptoms may include redness of the eye and discharge. The infection can be spread to other people and to both eyes.

Who should not use AzaSite?

Do not use AzaSite if you are allergic to azithromycin or any of the ingredients in AzaSite. See the end of this Patient Information leaflet for a complete list of the ingredients in AzaSite.

What should I tell my doctor before using AzaSite?

Before you use AzaSite, tell your doctor if you:

- wear contact lenses. Do not wear contact lenses if you have signs or symptoms of bacterial conjunctivitis.
- are pregnant or plan to become pregnant. Talk to your doctor if you are pregnant or plan to become pregnant.
- are breast-feeding or plan to breast-feed. AzaSite passes into your breast milk. Talk to your doctor about the best way to feed your baby if you are using AzaSite.

Tell your doctor about all the medicines you take, including prescription and non-prescription medicines, vitamins, and herbal supplements.

Know the medicines you take. Keep a list of them to show your doctors and pharmacist when you get a new medicine.

How should I use AzaSite?

- Read the Instructions for Use at the end of this Patient Information leaflet for the right way to use AzaSite.
- Use AzaSite exactly as your doctor tells you to use it.
- For the first 2 days place 1 drop of AzaSite in your eye (or eyes) each morning and 1 drop in your eye (or eyes) each evening. Wait 8 to 12 hours after placing your morning drops before you place evening drops in your eye (or eyes).
- For the next 5 days place 1 drop of AzaSite in your eye (or eyes) 1 time each day.
- Make sure you continue to use AzaSite as directed by your doctor even if you feel better after you start using it. Skipping drops can increase the chances that:
  - your medicine will not work well
  - Bacteria can develop resistance, which means in the future your bacterial conjunctivitis may not improve from AzaSite or other drugs that treat infections from bacteria.

What should I be aware of while using AzaSite?

Do not wear contact lenses if you have signs or symptoms of bacterial conjunctivitis and until you have finished your prescribed course of treatment. The symptoms of bacterial conjunctivitis may include:

- discharge coming from the eye
- eye redness
- eye irritation

Only your doctor can tell you if you have bacterial conjunctivitis.

Severe allergic reactions have been reported rarely when azithromycin has been taken by mouth.

- Serious rash or serious allergic reactions may occur. Azithromycin, the active ingredient in AzaSite, may cause a serious rash or a serious allergic reaction. Both of these reactions may need to be treated in a hospital and may be life-threatening.
- Stop taking AzaSite and call your doctor right away or get emergency help if you have any of these symptoms:
  - skin rash, hives, sores in your mouth, or your skin blisters and peels
  - swelling of your face, eyes, lips, tongue, or throat
  - trouble swallowing or breathing

Increased risk of other infections caused by bacteria or fungi.

- Using AzaSite for a long time may cause other bacteria or fungi to grow. If this happens you may get a new infection. Tell your doctor right away if your symptoms do not get better.

What are the possible side effects of AzaSite?

The most common side effect of AzaSite is eye irritation.

Other side effects seen with AzaSite include:

- eye burning, stinging and irritation when the drop hits your eye
- irritation on your eyelid and the skin around your eye
- a feeling of discomfort and irritation or that something is in your eye
- dry eye
- eye pain
- eye itching
- discharge coming from your eye
- changes to the surface of your eye
- blurred vision
- changes in your taste
- hives and rash on your skin
- stuffy nose and sinus infection
- swelling around your eye or of your face

Tell your doctor about any side effect that bothers you or that does not go away.

These are not all of the possible side effects of AzaSite. For more information, ask your doctor or pharmacist.

Call your doctor for medical advice about side effects. You may report side effects to FDA at 1-800-FDA-1088.

How should I store AzaSite?

- Before you open your AzaSite, store it in the refrigerator between 36°F to 46°F (2°C to 8°C).
- After you open your AzaSite, store it at room temperature or the refrigerator between 36°F to 77°F (2°C to 25°C)
- AzaSite should not be stored for more than 14 days after opening. After 14 days, throw the AzaSite bottle away.
- Safely throw away medicine that is out of date or no longer needed.

Keep AzaSite and all medicines out of reach of children.

General information about the safe and effective use of AzaSite

Medicines are sometimes prescribed for purposes other than those listed in a Patient Information leaflet. Do not use AzaSite for a condition for which it was not prescribed. Do not give AzaSite to other people, even if they have the same symptoms that you have. It may harm them.

This Patient Information summarizes the most important information about AzaSite. If you would like more information, talk with your doctor. You can ask your pharmacist or doctor for information about AzaSite that is written for health professionals.

For more information, call 1-833-838-4028.

What are the ingredients in AzaSite?

Active ingredient: azithromycin

Inactive ingredients: 0.003% benzalkonium chloride, mannitol, citric acid, sodium citrate, poloxamer 407, polycarbophil, edetate disodium (EDTA), sodium chloride, water, and sodium hydroxide.

Instructions for Use

AzaSite® (A-zuh-site)
(azithromycin ophthalmic solution) 1%

Read this Instructions for Use for AzaSite before you start using it and each time you get a refill. There may be new information. This leaflet does not take the place of talking to your doctor about your medical condition or treatment.

Important:

- AzaSite is for use as an eye drop only.

The checklist below tells you when to use your medicine for each eye that has bacterial conjunctivitis:

□ □ | Day 1: | 1 drop in the morning and 1 drop in the evening
□ □ | Day 2: | 1 drop in the morning and 1 drop in the evening
□ | Day 3 | 1 drop anytime during the day
□ | Day 4 | 1 drop anytime during the day
□ | Day 5 | 1 drop anytime during the day
□ | Day 6 | 1 drop anytime during the day
□ | Day 7 | 1 drop anytime during the day

This is a total of 9 drops of AzaSite for each infected eye.

- Avoid letting the applicator tip touch your eye, your fingers, or other objects.
- If a drop misses your eye, try again.
- Follow the steps below to use AzaSite correctly.

Before using a new bottle of AzaSite:
- Turn the white cap clockwise until it comes off. Throw away the white cap. See Figure A | - Hold the bottle straight, turn the tan cap counterclockwise until it comes off. Put the tan cap back on the bottle and close tightly. (This lets out the air.) See Figure B
Wash your hands each time you use AzaSite.
To use AzaSite:
Step 1. Turn the closed bottle upside down. See Figure C | Step 2. Shake your hand firmly. This helps move the medicine into the tip of the bottle. See Figure D
Step 3. Hold the bottle upside down and take off the tan cap. See Figure E | Step 4. Tilt your head back. Hold the bottle over your eye and gently squeeze the bottle to let 1 drop into each eye that has bacterial conjunctivitis. Put the tan cap back on the bottle and close tightly. See Figure F
If a drop does not come out of the bottle, repeat steps one to four.

Manufactured for: Thea Pharma Inc.
Waltham, MA 02451

U.S. Patent No.: 7,758,553

AzaSite is a registered trademark of Thea Pharma Inc.

DuraSite is a registered trademark of Sun Pharma.

© 2024. Thea Pharma Inc.
All rights reserved

This Patient Information and Instructions for Use have been approved by the U.S. Food and Drug Administration.

Revised: 07/2024

PRINCIPAL DISPLAY PANEL - 2.5 mL Bottle Carton

NDC 82584-307-03

AzaSITE®
(azithromycin ophthalmic solution) 1%

Sterile 2.5 mL

Rx Only

FOR OPHTHALMIC USE ONLY